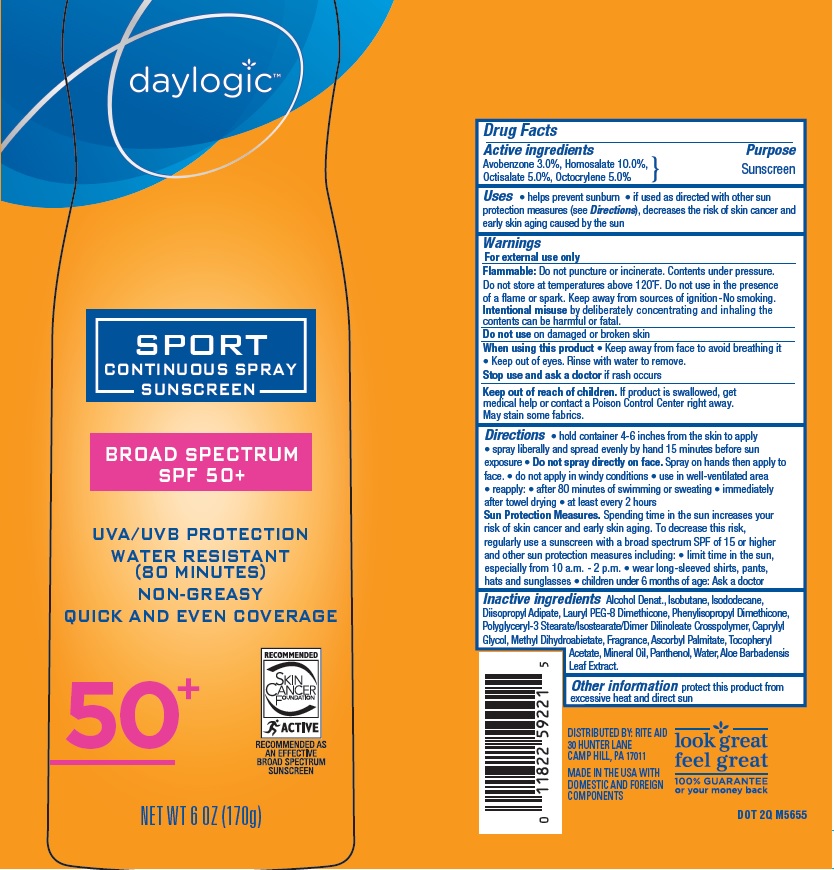 DRUG LABEL: Rite Aid Sport  
NDC: 11822-1820 | Form: SPRAY
Manufacturer: Rite Aid
Category: otc | Type: HUMAN OTC DRUG LABEL
Date: 20160308

ACTIVE INGREDIENTS: AVOBENZONE 3 g/100 g; HOMOSALATE 10 g/100 g; OCTISALATE 5 g/100 g; OCTOCRYLENE 5 g/100 g
INACTIVE INGREDIENTS: ALCOHOL; ISOBUTANE; ISODODECANE; DIISOPROPYL ADIPATE; CAPRYLYL GLYCOL; METHYL DIHYDROABIETATE; ASCORBYL PALMITATE; .ALPHA.-TOCOPHEROL ACETATE; MINERAL OIL; PANTHENOL; WATER; ALOE VERA LEAF

Drug Facts

Active Ingredients

Avobenzone 3.0%, Homosalate 10.0%, Octisalate 5.0%, Octocrylene 5.0%

Purpose

Sunscreen

Uses

- helps prevent sunburn
- if used as directed with other sun protection measures (see Directions), decreases the risk of skin cancer and early skin aging caused by the sun

Warnings

For external use only

Flammable: Do not puncture or incinerate. Contents under pressure. Do not store at temperatures above 120^0F. Do not use in the presence of a flame or spark. Keep away from sources of ignition-No smoking.

Intentional misuse by deliberately concentrating and inhaling the contents can be harmful or fatal.

Do not use

on damaged or broken skin

When using this product

- Keep away from face to avoid breathing it

- Keep out of eyes. Rinse with water to remove.

Stop use and ask a doctor

is rash occurs

Keep out of reach of children.

If product is swallowed, get medical help or contact a Poison Control Center right away.

- May stain some fabrics

Directions

- hold container 4-6 inches from the skin to apply
- spray liberally and spread evenly by hand 15 minutes before sun exposure
- Do not spray directly on face. Spray on hands then apply to face.
- do not apply in windy conditions
- use in well-ventilated area
- reapply:
- after 80 minutes of swimming or sweating
- immediately after towel drying
- at least every 2 hours

Sun Protection Measures. Spending time in the sun increases your risk of skin cancer and early skin aging. To decrease this risk, regularly use a sunscreen with a broad spectrum SPF of 15 or higher and other sun protection measures including:

- limit time in the sun, especially from 10 a.m.-2p.m.
- wear long-sleeve shirts, pants, hats and sunglasses
- children under 6 months of age: Ask a doctor.

Inactive Ingredients

Alcohol Denat., Isobutane, Isododecane, Diisopropyl Adipate, Lauryl PEG-8 Dimethicone, Phenylisopropyl Dimethicone, Polyglyceryl-3 Stearate/Isostearate/Dimer Dilinoleate Crosspolymer, Caprylyl Glycol, Methyl Dihydroabietate, Fragrance, Ascorbyl Palmitate, Tocopheryl Acetate, Mineral Oil, Panthenol, Water, Aloe Barbadensis Leaf Extract.

Other information

protect this product from excessive heat and direct sun

Principle Display Label

NDC: 11822-1820-4

daylogic

SPORT CONTINUOUS SPRAY

SUNSCREEN

BROAD SPECTRUM

SPF 50+

UVA/UVB PROTECTION

WATER RESISTANT

(80 MINUTES)

NON-GREASY

QUICK AND EVEN COVERAGE

50+

NET WT 6 OZ (170g)